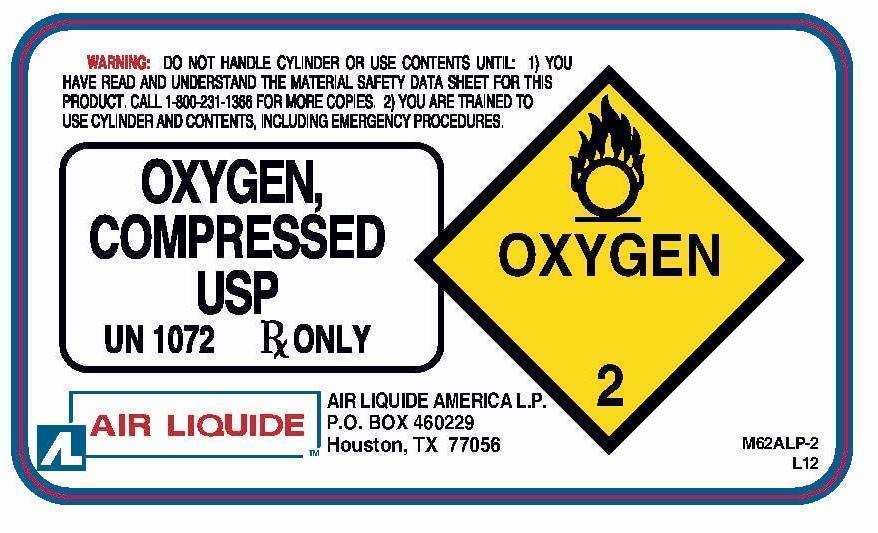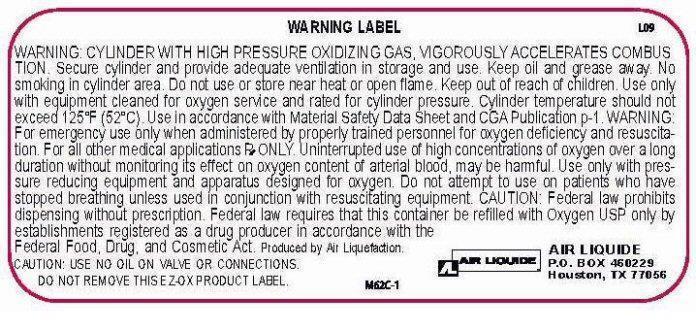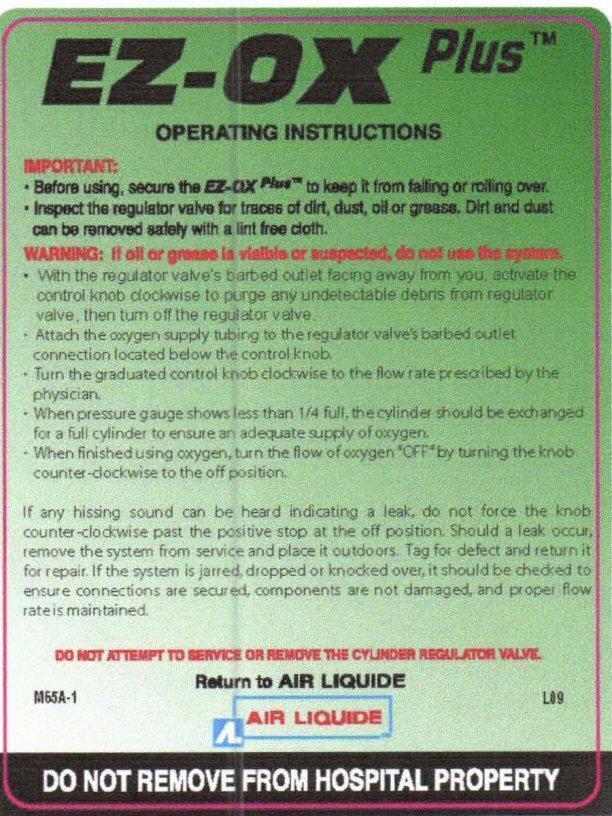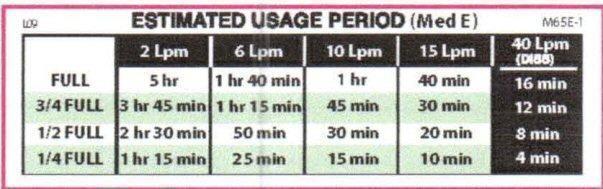 DRUG LABEL: EZ-OX Plus
                
NDC: 10671-101 | Form: GAS
Manufacturer: Air Liquide America L.P.
Category: prescription | Type: HUMAN PRESCRIPTION DRUG LABEL
Date: 20140115

ACTIVE INGREDIENTS: OXYGEN 99 L/100 L

OXYGEN COMPRESSED USP Label

WARNING: DO NOT HANDLE CYLINDER OR USE CONTENTS UNTIL 1) YOU HAVE READ AND UNDERSTAND THE MATERIAL SAFETY DATA SHEET FOR THIS PRODUCT. CALL 1-800-231-1366 FOR MORE COPIES. 2) YOU ARE TRAINED TO USE CYLINDER AND CONTENTS, INCLUDING EMERGENCY PROCEDURES.

OXYGEN COMPRESSED USP OXYGEN 2

UN 1072 Rx ONLY

AIR LIQUIDE

AIR LIQUIDE AMERICA L.P.
P.O. BOX 460229
Houston, TX 77056

M62ALP-2 L12

WARNING LABEL L09

WARNING: CYLINDER WITH HIGH PRESSURE OXIDIZING GAS, VIGOROUSLY ACCELERATES COMBUSTION. Secure cylinder and provide adequate ventilation in storage and use. Keep oil and grease away. No smoking in cylinder area. Do not use or store near heat or open flame. Keep out of reach of children. Use only with equipment cleaned for oxygen service and rated for cylinder pressure. Cylinder temperature should not exceed 125 F (52 C). Use in accordance with Material Safety Data Sheet and CGA Publication p-1. WARNING: For emergency use only when administered by properly trained personnel for oxygen deficiency and resuscitation. For all other medical applications Rx ONLY. Uninterrupted use of high concentrations of oxygen over a long duration without monitoring its effect on oxygen content of arterial blood, may be harmful. Use only with pressure reducing equipment and apparatus designed for oxygen. Do not attempt to use on patients who have stopped breathing unless used in conjunction with resuscitating equipment. CAUTION: Federal law prohibits dispensing without prescription. Federal law requires that this container be refilled with OXYGEN USP only by establishments registered as a drug producer in accordance with the Federal Food, Drug, and Cosmetic Act. Produced by Air Liquefaction. CAUTION: USE NO OIL ON VALVE OR CONNECTIONS. DO NOT REMOVE THIS EZ-OX PRODUCT LABEL.

M62C-1

AIR LIQUIDE
P.O.BOX 460229
Houston, TX 77056

EZ-OX Plus Label

EZ-OX Plus ™

OPERATING INSTRUCTIONS

IMPORTANT: · Before using secure the EZ-OX Plus™ to keep it from falling or rolling over.

· Inspect the regulator valve for traces of dirt, dust, oil or grease. Dirt and dust can be removed safely with a lint free cloth.

WARNING: If oil or grease is visible or suspected do not use the system.

· With the regulator valve's barbed outlet facing away from you, activate the control knob clockwise to purge any undetectable debris from the regulator valve, then turn off the regulator valve

· Attach the oxygen supply tubing to the regulator valve's barbed outlet connection located below the control knob.

· Turn the graduated knob clockwise to the flow rate prescribed by the physician

· When the pressure gauge shows less than1/4 full, the cylinder should be exchanged for a full cylinder to ensure an adequate supply of oxygen

· When finished using oxygen, turn the flow of oxygen to "OFF" by turning the knob counter-clockwise to the off position.

If any hissing sound can be heard indicating a leak, do not force the knob counter-clockwise past the positive stop at the off position. Should a leak occur, remove the system from service and place it outdoors. Tag for defect and return it for repair. If the system is jarred, dropped or knocked over, it should be checked to ensure connections are secured, components are not damaged, and proper flow rate is maintained.

DO NOT ATTEMPT TO SERVICE OR REMOVE THE CYLINDER REGULATOR VALVE

Return to AIR LIQUIDE
AIR LIQUIDE

M65A-1 L09

D NOT REMOVE FROM HOSPITAL PROPERTY